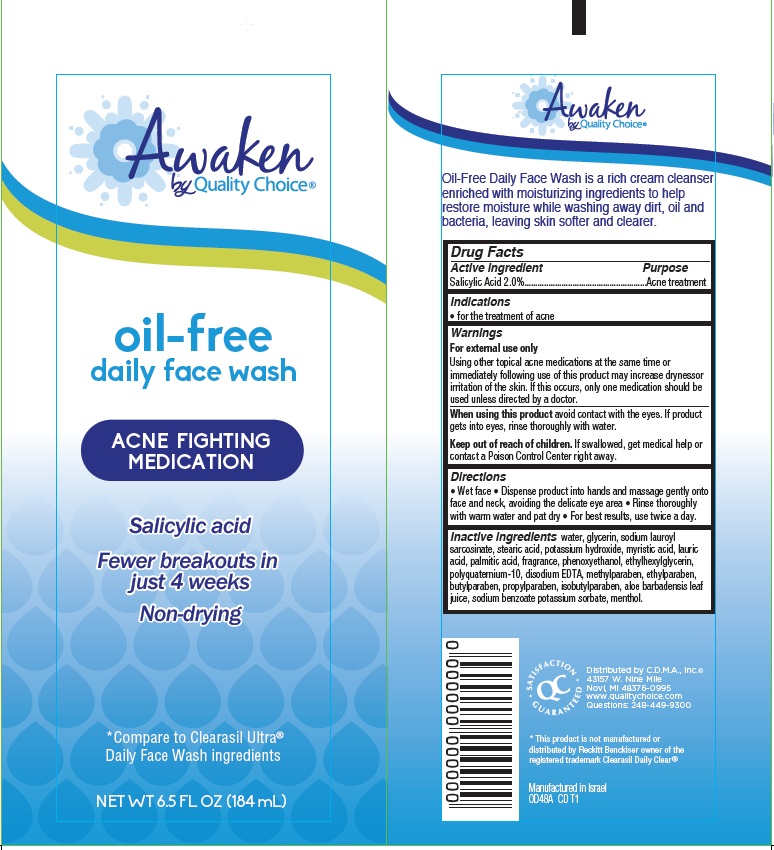 DRUG LABEL: Awaken Oil-Free Daily Face Wash
NDC: 63868-249 | Form: CREAM
Manufacturer: Chain Drug Marketing Association
Category: otc | Type: HUMAN OTC DRUG LABEL
Date: 20140918

ACTIVE INGREDIENTS: SALICYLIC ACID 2 g/100 mL
INACTIVE INGREDIENTS: WATER; GLYCERIN; SODIUM LAUROYL SARCOSINATE; STEARIC ACID; POTASSIUM HYDROXIDE; MYRISTIC ACID; LAURIC ACID; PALMITIC ACID; PHENOXYETHANOL; ETHYLHEXYLGLYCERIN; POLYQUATERNIUM-10 (1000 MPA.S AT 2%); EDETATE DISODIUM; METHYLPARABEN; ETHYLPARABEN; BUTYLPARABEN; PROPYLPARABEN; ISOBUTYLPARABEN; ALOE VERA LEAF; SODIUM BENZOATE; POTASSIUM SORBATE; MENTHOL

Awaken by Quality Choice® oil-free daily face wash

Active ingredient

Salicylic Acid 2.0%

Purpose

Acne Treatment

Indications

- for the treatment of acne

Warnings

For external use only.

Using other topical acne medications at the same time or immediately following use of this product may increase dryness or irritation of the skin. If this occurs, only one medication should be used unless directed by a doctor.

When using this product avoid contact with the eyes. If product gets into eyes, rinse thoroughly with water.

Keep Out of Reach of Children.

If swallowed, get medical help or contact a Poison Control Center right away.

Directions

- Wet face
- Dispense product into hands and massage gently onto face and neck, avoiding the delicate eye area
- Rinse thoroughly with warm water and pat dry
- For best results, use twice a day.

Other Information

Oil-Free Daily Face Wash is a rich cream cleanser enriched with moisturizing ingredients to help restore moisture while washing away dirt, oil and bacteria, leaving skin softer and clearer.

Inactive ingredients

water, glycerin, sodium lauroyl sarcosinate, stearic acid, potassium hydroxide, myristic acid, lauric acid, palmitic acid, fragrance, phenoxyethanol, ethylhexylglycerin, polyquaternium-10, disodium EDTA, methylparaben, ethylparaben, butylparaben, propylparaben, isobutylparaben, aloe barbadensis leaf juice, sodium benzoate, potassium sorbate, menthol.

Package/Label Principal Display Panel Awaken by Quality Choice® oil-free daily face wash Acne Fighting Medication Salicylic acid Fewer breakouts in just 4 weeks Non-drying *Compare to Clearasil Ultra® Daily Face Wash ingredients Net Wt 6.5 Fl Oz (184 mL) Distributed by C.D.M.A., Inc.® 43157 W. Nine Mile Novi, MI 48376-0995 Questions: 248-449-9300 *This product is not manufactured or distributed by Reckitt Benckiser owner of the registered trademark Clearasil Daily Clear®. Manufactured in Israel 0D48A CD T1

Carton Label